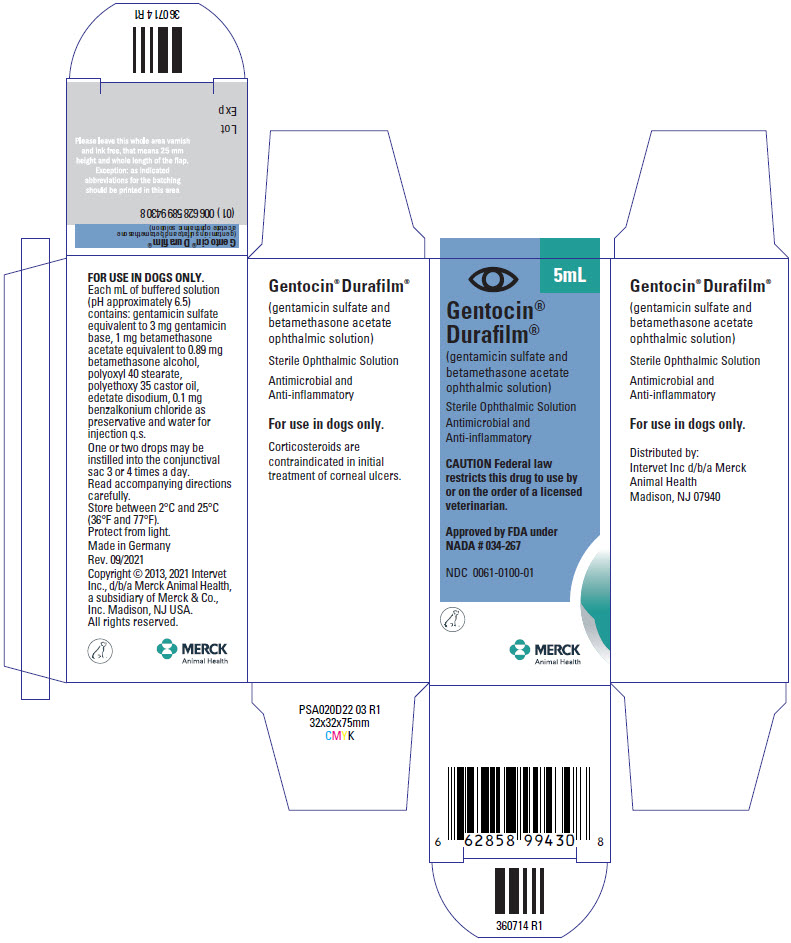 DRUG LABEL: Gentocin Durafilm
NDC: 0061-0100 | Form: SOLUTION
Manufacturer: Merck Sharp & Dohme Corp.
Category: animal | Type: PRESCRIPTION ANIMAL DRUG LABEL
Date: 20241115

ACTIVE INGREDIENTS: GENTAMICIN SULFATE 3 mg/1 mL; BETAMETHASONE ACETATE 0.89 mg/1 mL

Gentocin® Durafilm®
(gentamicin sulfate and betamethasone acetate ophthalmic solution)

Sterile Ophthalmic Solution
Antimicrobial and Anti-inflammatory

PRODUCT INFORMATION

Approved by FDA under NADA # 034-267

For Use in Dogs Only

CAUTION Federal law restricts this drug to use by or on the order of a licensed veterinarian.

DESCRIPTION

DESCRIPTION GENTOCIN DURAFILM Ophthalmic Solution is a sterile preparation for topical application. Each mL of buffered solution (pH approximately 6.5) contains gentamicin sulfate equivalent to 3 mg gentamicin base, 1 mg betamethasone acetate equivalent to 0.89 mg betamethasone alcohol, polyoxyl 40 stearate, polyethoxy 35 castor oil, edetate disodium, 0.1 mg benzalkonium chloride as preservative and water for injection q.s.

Gentamicin is a bactericidal antibiotic of the aminoglycoside group derived from Micromonospora purpurea of the Actinomyces group. It is a powder, white to buff in color, basic in nature, readily soluble in water and highly stable in solution.

Betamethasone, a synthetic derivative of prednisolone, is 9-alpha-fluoro-16-beta-methyl-prednisolone.

VETERINARY INDICATIONS

INDICATIONS GENTOCIN DURAFILM Ophthalmic Solution is indicated for the treatment of external eye infections and inflammation in dogs.

Clinical reports indicate it is useful for the management of some cases of pigmentary keratitis and pannus. Temporary remission of some of the pathological lesions of the aforementioned conditions have been noted following therapy with GENTOCIN DURAFILM Ophthalmic Solution.

DOSAGE AND ADMINISTRATION The topical application of GENTOCIN DURAFILM Ophthalmic Solution should, in each instance, be administered to meet the specific needs of the individual case. One or two drops of the solution may be instilled into the conjunctival sac three or four times a day. Thereafter, the frequency of the dosage may be reduced but care should be taken not to discontinue therapy prematurely. In chronic conditions, withdrawal of treatment should be carried out by gradually decreasing the frequency of application.

CONTRAINDICATIONS

CONTRAINDICATIONS Corticosteroids are contraindicated in initial treatment of corneal ulcers.

GENTOCIN DURAFILM Ophthalmic Solution is contraindicated in ocular conditions where there is deep ulceration without vascularization and in conditions of viral origin before healing has commenced.

WARNINGS

WARNINGS Not for human use. Keep this and all drugs out of the reach of children. Clinical and experimental data have demonstrated that corticosteroids administered orally or parenterally to animals may induce the first stage of parturition when administered during the last trimester of pregnancy and may precipitate premature parturition followed by dystocia, fetal death, retained placenta, and metritis.

Additionally, corticosteroids administered to dogs, rabbits, and rodents during pregnancy have produced cleft palate. Other congenital anomalies including deformed forelegs, phocomelia, and anasarca have been reported in offspring of dogs which received corticosteroids during pregnancy.

PRECAUTIONS

PRECAUTIONS The antibiotic sensitivity of the infective organism in bacterial conjunctivitis should be determined prior to the use of this preparation. The preparation is contraindicated in the case of nonsusceptible microorganisms. In deep-seated infections or when systemic infection threatens, specific systemic antibiotic or sulfonamide therapy should be employed.

Extended use of topical corticosteroids may cause increased intraocular pressure in susceptible patients. In prolonged therapy, it is advisable to measure intraocular pressure. In human medicine, in diseases that cause thinning of the cornea, perforation has been known to have occurred with the use of topical steroids.

Use of corticosteroids, depending on dose, duration, and specific steroid, may result in inhibition of endogenous steroid production following drug withdrawal. In patients presently receiving or recently withdrawn from systemic corticosteroid treatments, therapy with a rapidly acting corticosteroid should be considered in especially stressful situations.

ADVERSE REACTIONS

ADVERSE REACTIONS SAP and SGPT (ALT) enzyme elevations, polydipsia, and polyuria have occurred following parenteral or systemic use of synthetic corticosteroids in dogs. Vomiting and diarrhea (occasionally bloody) have been observed in dogs.

Cushing's syndrome in dogs has been reported in association with prolonged or repeated steroid therapy.

A transient stinging sensation, usually expressed as some form of resentment by the animal, following topical application of the drug, has been noted in a small number of cases. Usually this does not require discontinuance of therapy.

To report an adverse reaction, product-related problem, or human exposure, please call Merck Animal Health Technical Services at 1-800-224-5318.

To obtain a copy of the Material Safety Data Sheet (MSDS), call 1-800-770-8878.

For additional information about adverse drug experience reporting for animal drugs, contact FDA at 1-888-FDA-VETS or http://www.fda.gov/reportanimalae

CLINICAL PHARMACOLOGY

CLINICAL PHARMACOLOGY GENTOCIN DURAFILM Ophthalmic Solution incorporates polyoxyl 40 stearate and polyethoxy 35 castor oil which provide a colloidal dispersion of active ingredients. This aqueous colloidal solution offers specific advantages in treating eye conditions. DURAFILM covers the conjunctiva with a thin, clear, quickly spreading film which carries therapeutic components to accessible structures and maintains prolonged contact.

GENTOCIN DURAFILM Ophthalmic Solution provides the antibacterial properties of gentamicin sulfate plus the anti-inflammatory action of betamethasone acetate.

Gentamicin sulfate, a wide-spectrum antibiotic, is a highly effective topical treatment in primary and secondary bacterial infections of the eye and surrounding tissues. Gentamicin is bactericidal in vitro against a wide variety of gram-positive and gram-negative bacteria. Concentrations of gentamicin sulfate required to inhibit growth of gram positive and gram-negative clinical and laboratory strains of bacteria tested were less than those of neomycin in most instances.^1. Gentamicin is active against most gram-negative bacteria including Pseudomonas aeruginosa, indole positive and negative Proteus species, Escherichia coli, Kiebsiella pneumoniae, Aerobacter aerogenes, and Neisseria. Gentamicin is also active against strains of gram-positive bacteria including Staphylococcus species and Group A Beta-Hemolytic Streptococci.

Betamethasone produces hormonal and metabolic effects common to all adrenocortical steroids, and in low dosage affords anti-inflammatory, anti-allergic, and anti-rheumatic effects. Studies in man show the glucocorticoid activity of betamethasone to be 10 to 15 times greater than prednisone. Betamethasone helps control excessive tissue reaction to infections, allergens, and trauma. The corticoids control the inflammatory and exudate phases of eye conditions, particularly those affecting the anterior chamber and external structure of the eye. However, they do not curtail the growth of the causative organisms. Betamethasone therapy may reduce the damaging sequelae in certain eye diseases and injuries as well as scarring and vascularization, and appears to alter the usual tissue response to injury. In initial acute phases of inflammation, local application of betamethasone provides prompt, symptomatic relief, accomplishing temporary control of the exudative phase, whether of bacterial, allergic, or traumatic origin.

Betamethasone also inhibits fibroblast formation during tissue repair.

ANIMAL SAFETY In a target animal safety study, GENTOCIN DURAFILM Ophthalmic Solution was administered for 14 consecutive days to healthy Beagle dogs at a dose of 2 drops/eye 4 times daily (1× maximum daily dose; 8 dogs), 4 drops/eye 4 times daily (2× maximum daily dose; 8 dogs), and 6 drops/eye (3× maximum daily dose; 8 dogs). Eight dogs received 6 drops of sterile saline/eye 4 times daily (Control 0×). A mild serous ocular discharge was observed in GENTOCIN DURAFILM treated dogs in a dose-related manner; which resolved within a few hours of dosing. Mild bilateral scleral redness was seen in the 2× and 3× groups between Days 4-8 which spontaneously resolved. Polyuria was evident in 1 of 8 dogs in the 3× group on Day 2, and was evident in a dose proportional manner in all three treatment groups after 14 days of dosing- 1× group (3 of 8 dogs), 2× group (7 of 8 dogs) and 3× group (8 of 8 dogs). In dogs from each GENTOCIN DURAFILM treated group, changes in hematological parameters included neutrophilia, lymphopenia, eosinopenia and decreased reticulocytes, and changes in blood chemistries included increased ALT, SAP, GGT, triglycerides, albumin, globulin and total protein levels and decreased CK levels. Urine specific gravity was decreased in each GENTOCIN DURAFILM treated group. Dogs in the GENTOCIN DURAFILM treated groups also had increased food consumption compared to dogs in the control group.

HOW SUPPLIED

HOW SUPPLIED GENTOCIN DURAFILM Ophthalmic Solution, is supplied in 10 mL squeeze dropper bottles with a 5 mL fill, in banded units of 10, NDC 0061 -0100-01.

STORAGE AND HANDLING

Store between 2° and 25°C (36° and 77°F).

Protect from light.

REFERENCES

REFERENCE

^1. Weinstein MJ, Luedemann GM, oden eM, Wagman GH. Gentamicin, a new broad-spectrum antibiotic complex. Antimicrob Agents and Chemother. 1963:1—7.

Made in Germany
Rev. 09/2021
Copyright © 2013, 2021 Intervet Inc., d/b/a Merck Animal Health, a subsidiary of Merck & Co., Inc. Madison, NJ USA. All rights reserved.

Distributed by:
Intervet Inc d/b/a Merck Animal Health
Madison, NJ 07940

369478 R1

PRINCIPAL DISPLAY PANEL - 5 mL Bottle Carton

5mL

Gentocin®
Durafilm®

(gentamicin sulfate and
betamethasone acetate
ophthalmic solution)

Sterile Ophthalmic Solution
Antimicrobial and
Anti-inflammatory

CAUTION Federal law
restricts this drug to use by
or on the order of a licensed
veterinarian.

Approved by FDA under
NADA # 034-267

NDC 0061-0100-01

MERCK
Animal Health